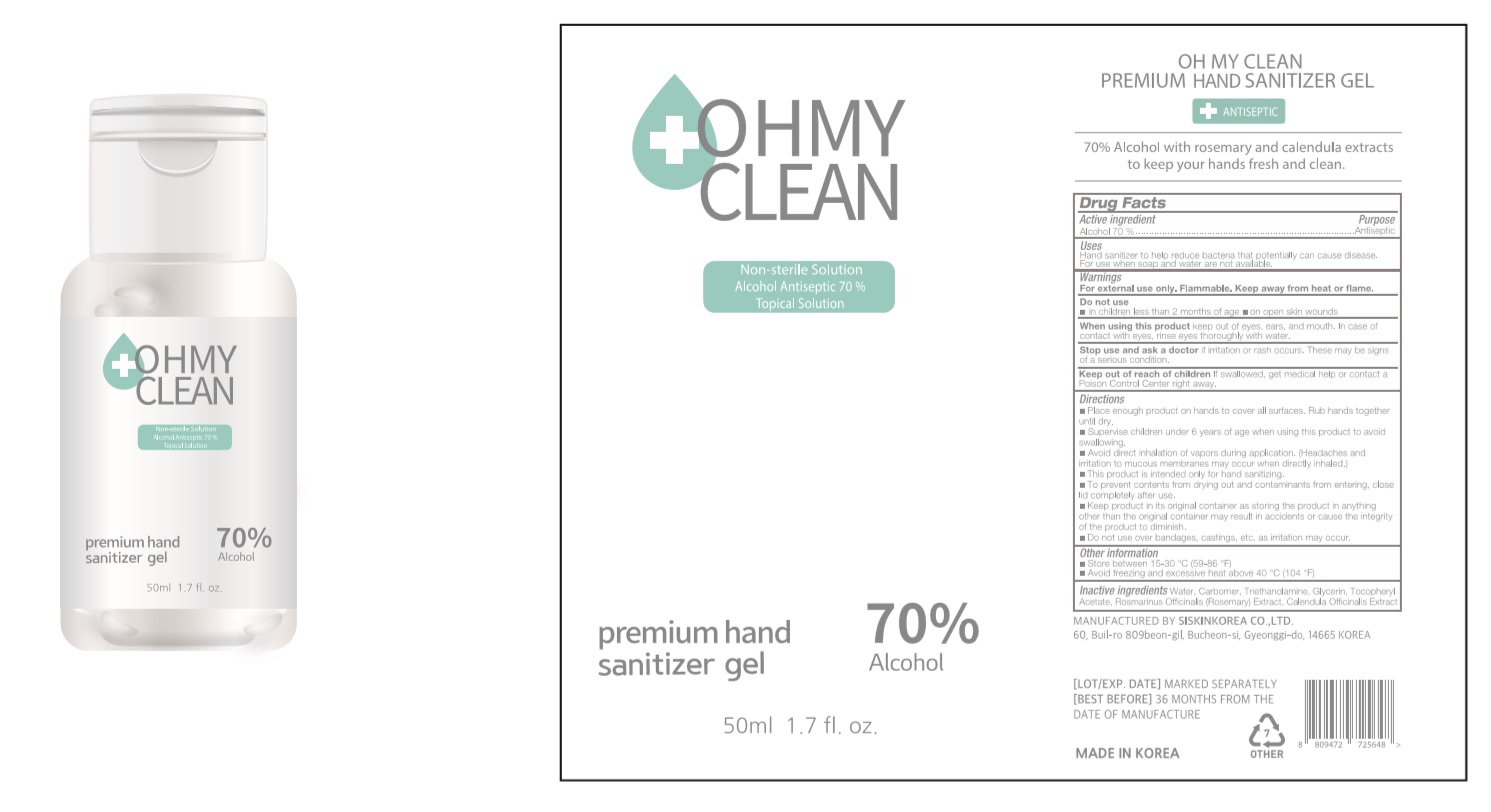 DRUG LABEL: OH MY CLEAN Premium Hand Sanitizer gel
NDC: 74514-7057 | Form: GEL
Manufacturer: SISKINKOREA CO.,LTD.
Category: otc | Type: HUMAN OTC DRUG LABEL
Date: 20200712

ACTIVE INGREDIENTS: ALCOHOL 35 mL/50 mL
INACTIVE INGREDIENTS: TROLAMINE; GLYCERIN; .ALPHA.-TOCOPHEROL ACETATE; CALENDULA OFFICINALIS WHOLE; WATER; ROSEMARY; CARBOMER HOMOPOLYMER, UNSPECIFIED TYPE

50ml_70%_gel_OH MY CLEAN Premium Hand Sanitizer gel